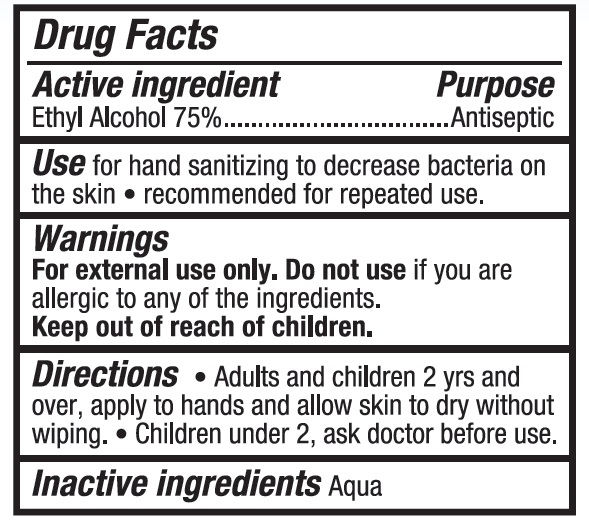 DRUG LABEL: HAND SANITIZING WIPES
NDC: 77720-002 | Form: CLOTH
Manufacturer: Skaffles Group Limited Liability Company
Category: otc | Type: HUMAN OTC DRUG LABEL
Date: 20200622

ACTIVE INGREDIENTS: ALCOHOL 75 mL/100 mL
INACTIVE INGREDIENTS: WATER

77720-002 HAND SANITIZING WIPES 75%Ethyl Alcohol

Active Ingredient

Ethyl Alcohol 75%

Purpose

Antiseptic

USE

For hand washing to decrease bacteria on the skin.
Recommended for repeated use.

Warning

For external use only. Do not use if you are allergic to
any of the ingredients.

Keep out of reach of children.

Directions

Directions● Adults and children 2 yrs and over,
apply to hands and allow skin to dry without wiping.
●Children under 2, ask doctor before use.

Inactive ingredients

aqua